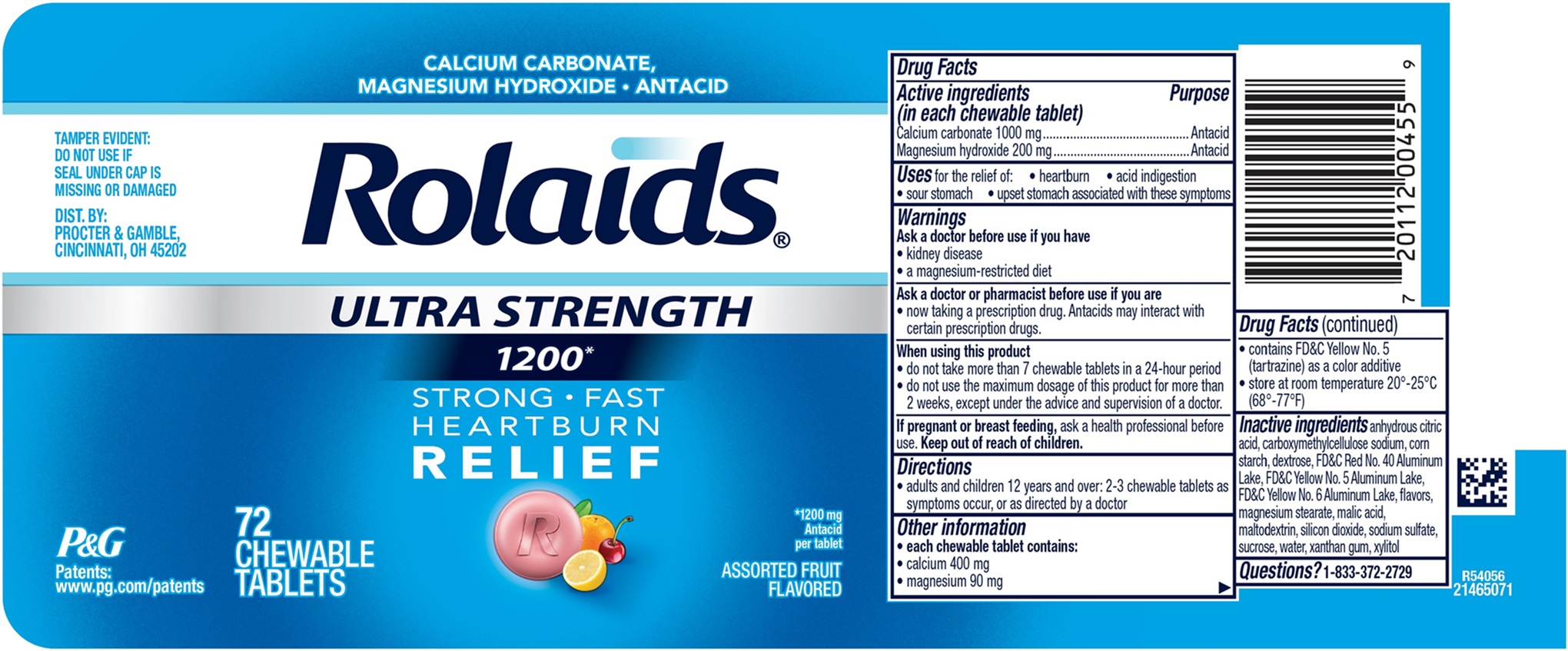 DRUG LABEL: Rolaids Ultra Strength 1200
NDC: 84126-322 | Form: TABLET, CHEWABLE
Manufacturer: THE PROCTER & GAMBLE MANUFACTURING COMPANY
Category: otc | Type: HUMAN OTC DRUG LABEL
Date: 20251202

ACTIVE INGREDIENTS: CALCIUM CARBONATE 1000 mg/1 1; MAGNESIUM HYDROXIDE 200 mg/1 1
INACTIVE INGREDIENTS: FD&C YELLOW NO. 5 ALUMINUM LAKE; FD&C YELLOW NO. 6 ALUMINUM LAKE; SILICON DIOXIDE; DEXTROSE; MAGNESIUM STEARATE; SODIUM SULFATE; SUCROSE; MALTODEXTRIN; WATER; XANTHAN GUM; STARCH, CORN; CARBOXYMETHYLCELLULOSE SODIUM; XYLITOL; ANHYDROUS CITRIC ACID; MALIC ACID; FD&C RED NO. 40 ALUMINUM LAKE

Rolaids ULTRA STRENGTH 1200

Drug Facts

Rolaids ULTRA STRENGTH 1200

Active ingredient

(in each chewable tablet)
Calcium carbonate 1000 mg
Magnesium hydroxide 200 mg

Purpose

Antacid

Antacid

Uses

for the relief of:

- heartburn
- acid indigestion
- sour stomach
- upset stomach associated with these symptoms

Warnings

Ask a doctor before use if you have

- kidney disease
- a magnesium-retricted diet

Ask a doctor or pharmacist before use if you are

- now taking a prescription drug. Antacids may interact with certain prescription drugs.

When using this product

- do not take more than 7 tablets in a 24-hour period
- do not use the maximum dosage for more than 2 weeks, except under the advice and supervision of a doctor.

Directions

- adults and children 12 years and over: 2-3 chewable tablets as symptoms occur, or as directed by a doctor.

Other information

- each chewable tablet contains:
- calcium 400 mg
- magnesium 90 mg
- contains FD&C Yellow No. 5 (tartrazine) as color additive
- store at room temperature 20° -25°C (68° -77°F)

Inactive ingredients

anhydrous citric acid, carboxymethylcellulose sodium, corn starch, dextrose, FD&C Red No. 40 Aluminum Lake, FD&C Yellow No. 5 Aluminum Lake, FD&C Yellow No. 6 Aluminum Lake, flavors, magnesium stearate, malic acid, maltodextrin, silicon dioxide, sodium sulfate, sucrose, water, xanthan gum, xylitol

Questions?

1-833-372-2729

TAMPER EVIDENT:

DO NOT USE IF SEAL UNDER CAP IS MISSING OR DAMAGED.

DIST. BY: PROCTER & GAMBLE, CINCINNATI, OH 45202

PRINCIPAL DISPLAY PANEL

CALCIUM CARBONATE, MAGNESIUM HYDROXIDE • ANTACID

Rolaids

ULTRA STRENGTH

1200*

STRONG • FAST

HEARTBURN

RELIEF

*1200 mg Antacid per tablet

ASSORTED FRUIT FLAVOR

72 CHEWABLE TABLETS